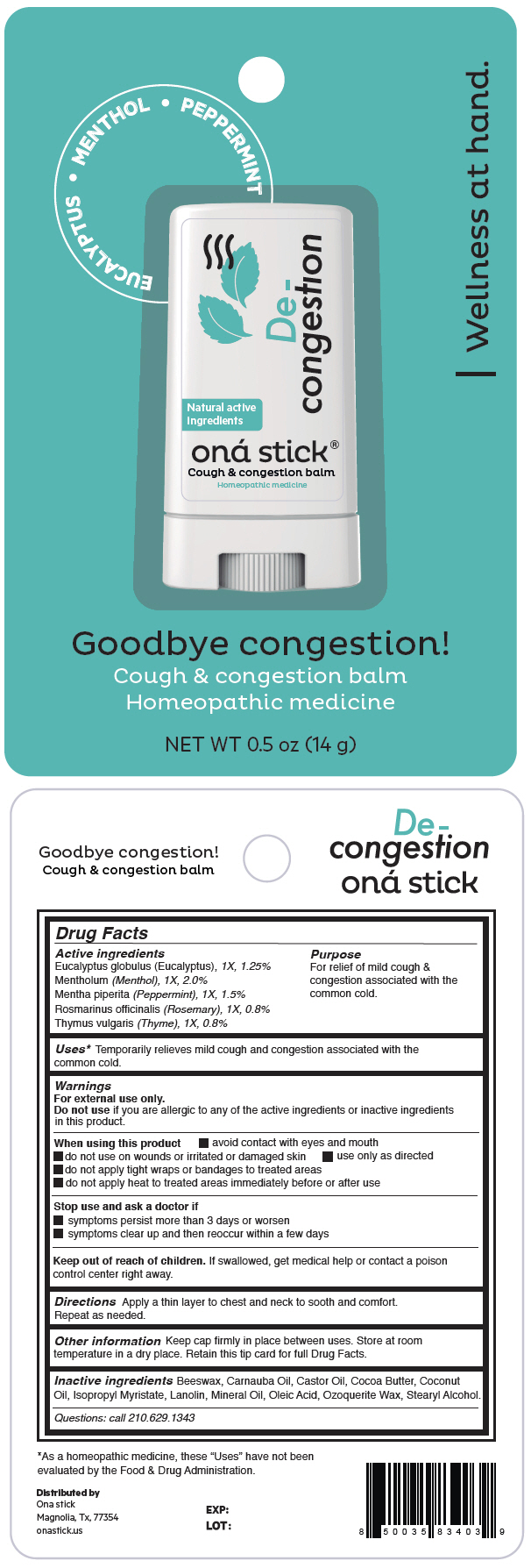 DRUG LABEL: De-congestion
NDC: 82610-004 | Form: STICK
Manufacturer: ONA STICK USA LLC
Category: homeopathic | Type: HUMAN OTC DRUG LABEL
Date: 20220317

ACTIVE INGREDIENTS: EUCALYPTUS GLOBULUS LEAF 1 [hp_X]/14 g; MENTHOL, UNSPECIFIED FORM 1 [hp_X]/14 g; PEPPERMINT 1 [hp_X]/14 g; ROSEMARY 1 [hp_X]/14 g; THYMUS VULGARIS LEAF 1 [hp_X]/14 g
INACTIVE INGREDIENTS: YELLOW WAX; CARNAUBA WAX; Castor Oil; Cocoa Butter; Coconut Oil; Isopropyl Myristate; Lanolin; Mineral Oil; Oleic Acid; CERESIN; Stearyl Alcohol

De-congestion

Drug Facts

ACTIVE INGREDIENT

Active ingredients | Purpose
Eucalyptus globulus (Eucalyptus), 1X, 1.25% Mentholum (Menthol), 1X, 2.0% Mentha piperita (Peppermint), 1X, 1.5% Rosmarinus officinalis (Rosemary), 1X, 0.8% Thymus vulgaris (Thyme), 1X, 0.8% | For relief of mild cough & congestion associated with the common cold.

Uses [As a homeopathic medicine, these "Uses" have not been evaluated by the Food & Drug Administration.]

Temporarily relieves mild cough and congestion associated with the common cold.

Warnings

For external use only.

Do not use if you are allergic to any of the active ingredients or inactive ingredients in this product.

When using this product

- avoid contact with eyes and mouth
- do not use on wounds or irritated or damaged skin
- use only as directed
- do not apply tight wraps or bandages to treated areas
- do not apply heat to treated areas immediately before or after use

Stop use and ask a doctor if

- symptoms persist more than 3 days or worsen
- symptoms clear up and then reoccur within a few days

Keep out of reach of children. If swallowed, get medical help or contact a poison control center right away.

Directions

Apply a thin layer to chest and neck to sooth and comfort. Repeat as needed.

Other information

Keep cap firmly in place between uses. Store at room temperature in a dry place. Retain this tip card for full Drug Facts.

Inactive ingredients

Beeswax, Carnauba Oil, Castor Oil, Cocoa Butter, Coconut Oil, Isopropyl Myristate, Lanolin, Mineral Oil, Oleic Acid, Ozoquerite Wax, Stearyl Alcohol.

Questions

call 210.629.1343

Distributed by
Ona stick
Magnolia, Tx, 77354

PRINCIPAL DISPLAY PANEL - 14 g Tube Blister Pack

EUCALYPTUS • MENTHOL • PEPPERMINT

Natural active
ingredients

De-
congestion

oná stick®
Cough & congestion balm
Homeopathic medicine

| Wellness at hand.

Goodbye congestion!

Cough & congestion balm
Homeopathic medicine

NET WT 0.5 oz (14 g)